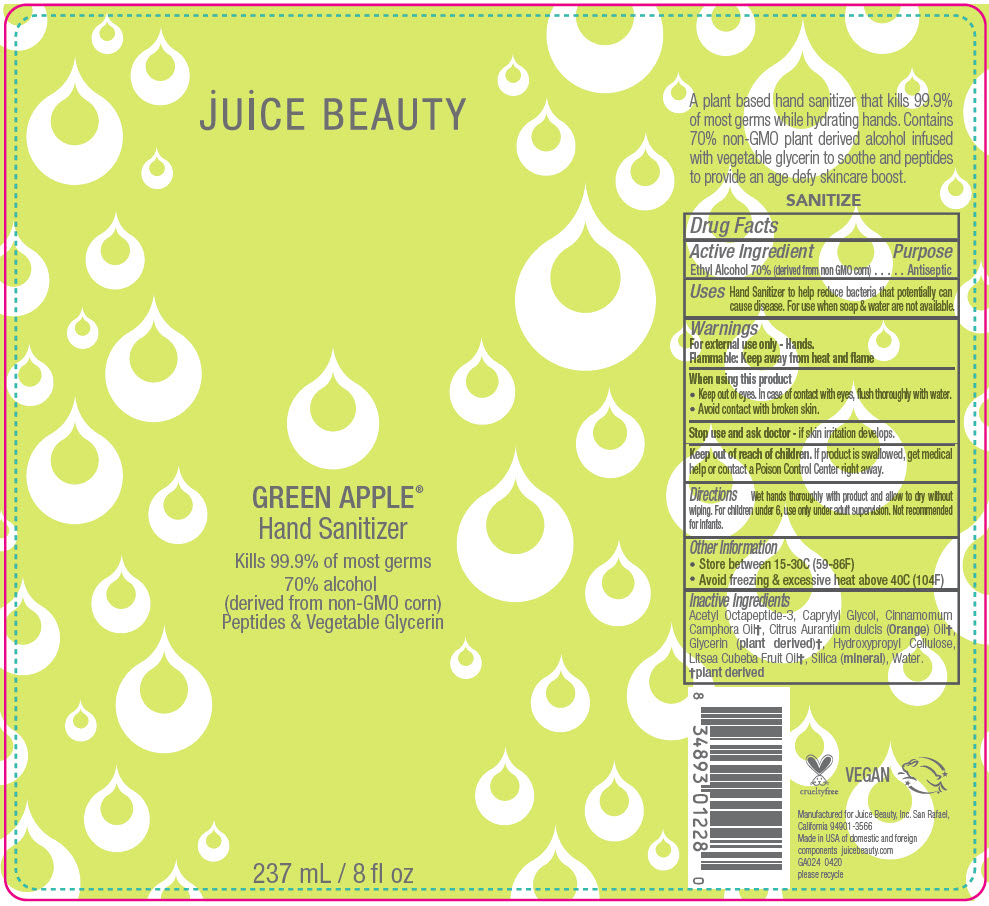 DRUG LABEL: GREEN APPLE HAND SANITIZER
NDC: 55165-0203 | Form: GEL
Manufacturer: Juice Beauty
Category: otc | Type: HUMAN OTC DRUG LABEL
Date: 20230106

ACTIVE INGREDIENTS: Alcohol 70 mL/100 mL
INACTIVE INGREDIENTS: acetyl octapeptide-3; Caprylyl glycol; CAMPHOR OIL; ORANGE OIL, COLD PRESSED; Glycerin; HYDROXYPROPYL CELLULOSE, UNSPECIFIED; LITSEA OIL; Silicon Dioxide; Water

GREEN APPLE® HAND SANITIZER

Drug Facts

Active Ingredient

Ethyl Alcohol 70% (derived from non GMO corn)

Purpose

Antiseptic

Uses

Hand Sanitizer to help reduce bacteria that potentially can cause disease. For use when soap & water are not available.

Warnings

For external use only - Hands.

Flammable: Keep away from heat and flame

When using this product

- Keep out of eyes. In case of contact with eyes, flush thoroughly with water.
- Avoid contact with broken skin.

Stop use and ask doctor - if skin irritation develops.

Keep out of reach of children. If product is swallowed, get medical help or contact a Poison Control Center right away.

Directions

Wet hands thoroughly with product and allow to dry without wiping. For children under 6, use only under adult supervision. Not recommended for infants.

Other Information

- Store between 15-30C (59-86F)
- Avoid freezing & excessive heat above 40C (104F)

Inactive Ingredients

Acetyl Octapeptide-3, Caprylyl Glycol, Cinnamomum Camphora Oil [plant derived] , Citrus Aurantium dulcis (Orange) Oil, Glycerin (plant derived), Hydroxypropyl Cellulose, Litsea Cubeba Fruit Oil, Silica (mineral), Water.

PRINCIPAL DISPLAY PANEL - 237 mL Bottle Label

juice BEAUTY

GREEN APPLE®
Hand Sanitizer

Kills 99.9% of most germs
70% alcohol
(derived from non-GMO corn)
Peptides & Vegetable Glycerin

237 mL / 8 fl oz